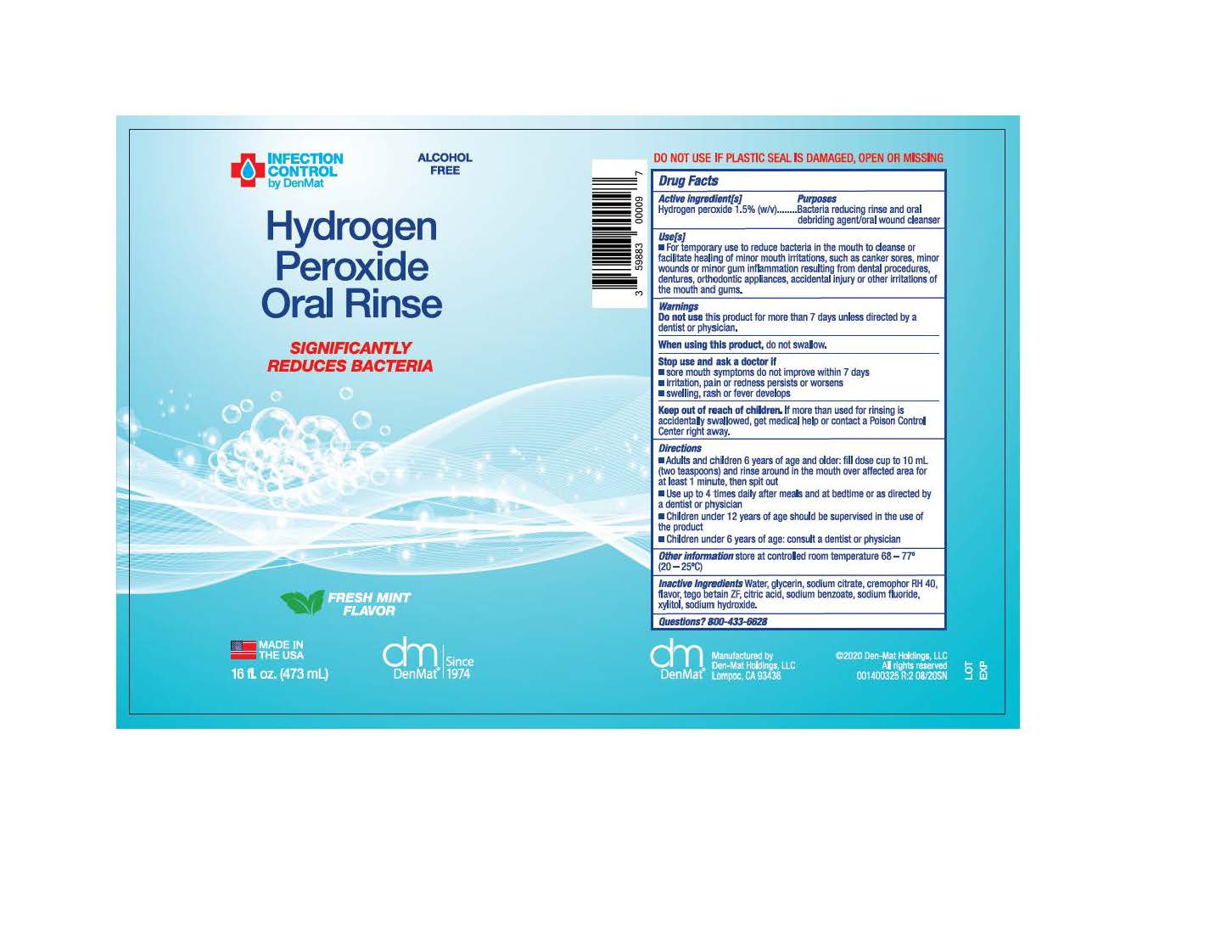 DRUG LABEL: Hydrogen Peroxide Oral Rinse
NDC: 59883-201 | Form: LIQUID
Manufacturer: Den-Mat Holdings, LLC
Category: otc | Type: HUMAN OTC DRUG LABEL
Date: 20200819

ACTIVE INGREDIENTS: HYDROGEN PEROXIDE 15 mg/1 mL
INACTIVE INGREDIENTS: SODIUM FLUORIDE; COCAMIDOPROPYL BETAINE; POLYOXYL 40 CASTOR OIL; CITRIC ACID MONOHYDRATE; SODIUM BENZOATE; XYLITOL; SODIUM HYDROXIDE; MINT; GLYCERIN; WATER; SODIUM CITRATE

ACTIVE INGREDIENT

Hydrogen peroxide 1.5% (w/v)

PURPOSE

Bacteria reducing rinse and oral debriding agent/oral wound cleanser

INDICATIONS AND USAGE

For temporary use to reduce bacteria in the mouth before and after dental procedures. Other uses include removal of oral debris and cleansing or healing of minor mouth irritations, such as canker sores, minor wounds and minor gum inflammation resulting from dental procedures, dentures, orthodontic appliances, accidental injury or other irritations of the mouth and gums.

Do not use this product for more than 7 days unless directed by a dentist or physician.

WHEN USING

do not swallow

Stop use and ask a doctor if

- sore mouth symptoms do not improve within 7 days
- irritation, pain or redness persists or worsens
- swelling, rash or fever develops

KEEP OUT OF REACH OF CHILDREN

If more than used for rinsing is accidentally swallowed, get medical help or contact a Poison Control Center right away.

Directions

- Adults and children 6 years of age and older: fill dose cup to 10 mL (two teaspoons) and rinse around in the mouth over affected area for at least 1 minute, then spit out.
- Use up to 4 times daily after meals and at bedtime or as directed by a dentist or physician
- Children under 12 years of age should be supervised in the use of the product
- Children under 6 years of age: consult a dentist or physician

Other Information

store at controlled room temperature 68-77° (20-25°C)

INACTIVE INGREDIENT

Water, glycerin, sodium citrate, cremophor RH 40, flavor, tego betain ZF, citric acid, sodium benzoate, sodium fluoride, xylitol, sodium hydroxide

QUESTIONS

800-433-6628